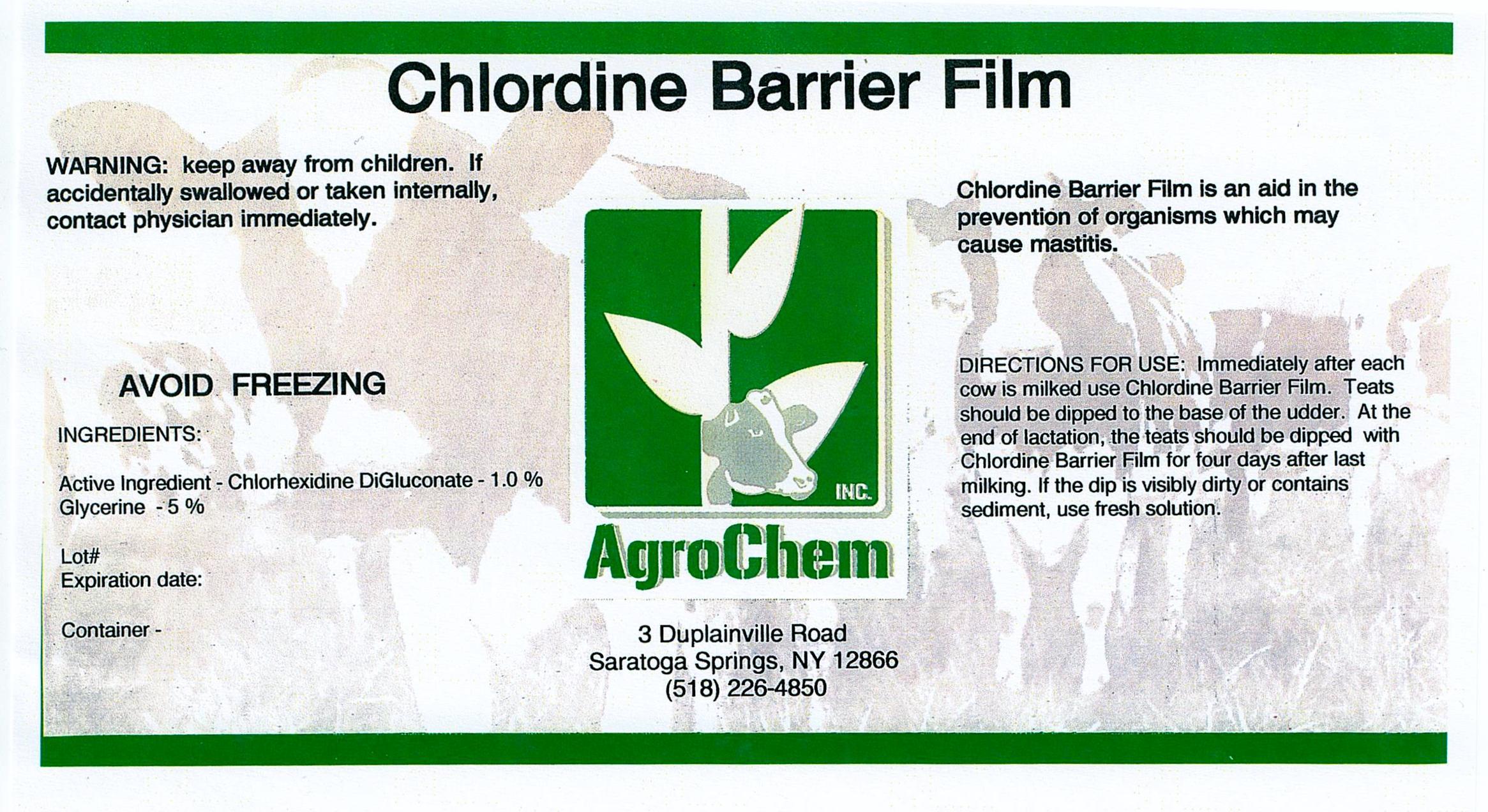 DRUG LABEL: Chlordine Barrier Film
NDC: 17307-3313 | Form: SOLUTION
Manufacturer: AgroChem Inc
Category: animal | Type: OTC ANIMAL DRUG LABEL
Date: 20131029

ACTIVE INGREDIENTS: CHLORHEXIDINE GLUCONATE 0.01 kg/1 kg
INACTIVE INGREDIENTS: POLYVINYL ALCOHOL 0.06 kg/1 kg; GLYCERIN 0.05 kg/1 kg; NONOXYNOL-12 0.01 kg/1 kg; ISOPROPYL ALCOHOL 0.04 kg/1 kg

Chlordine Barrier Film

WARNINGS AND PRECAUTIONS

WARNING: keep away from children. If

accidentally swallowed or taken internally,

contact physiciain immediately.

AVOID FREEZING

ACTIVE INGREDIENT

INGREDIENTS:

Active Ingredient – Chlorhexidine DiGluconate – 1.0%

Glycerine – 5%

DESCRIPTION

Chlordine Barrier Film is an aid in the

prevention of organisms which may

cause mastitis.

DIRECTIONS FOR USE: Immediately after each

cow is milked use Chlordine Barrier Film. Teats

should be dipped to the base of the udder. At the

end of lactation, the teats should be dipped with

Chlordine Barrier Film for four days after last

milking. If the dip is visibly dirty or contains

sediment, use fresh solution.